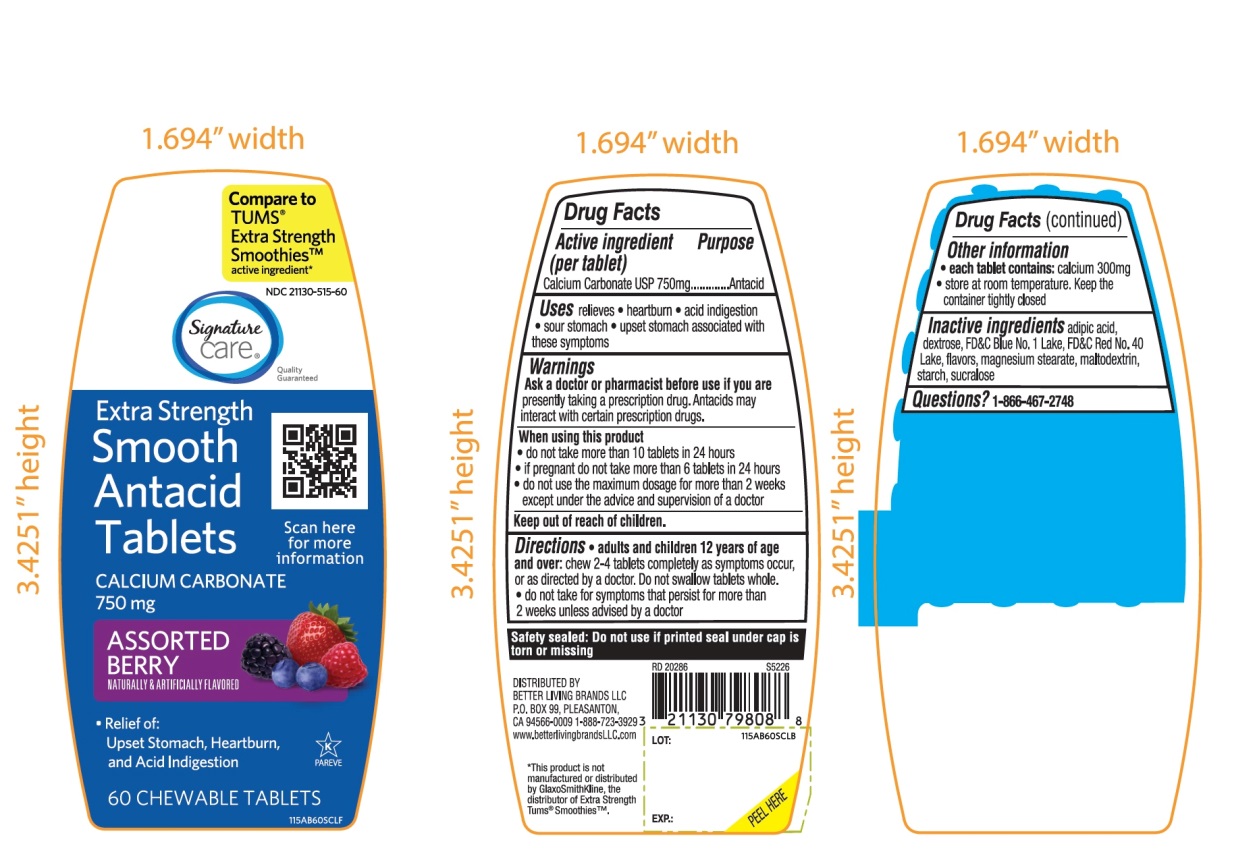 DRUG LABEL: Extra Strength Smooth
NDC: 21130-515 | Form: TABLET, CHEWABLE
Manufacturer: SAFEWAY
Category: otc | Type: HUMAN OTC DRUG LABEL
Date: 20251029

ACTIVE INGREDIENTS: CALCIUM CARBONATE 750 mg/1 1
INACTIVE INGREDIENTS: ADIPIC ACID; DEXTROSE, UNSPECIFIED FORM; FD&C BLUE NO. 1; FD&C RED NO. 40; MAGNESIUM STEARATE; MALTODEXTRIN; STARCH, CORN; SUCRALOSE

Extra Strength Smooth Antacid Calcium Carbonate Tablets

Active ingredient (per tablet)

Calcium Carbonate USP 750mg

Purpose

Antacid

Uses

relieves

- heartburn
- acid indigestion
- sour stomach
- upset stomach associated with these symptoms

Warnings

Ask a doctor or pharmacist before use if you arepresently taking a prescription drug. Antacids may interact with certain prescription drugs.

When using this product

- do not take more than 10 tablets in 24 hours
- if pregnant do not take more than 6 tablets in 24 hours
- do not use the maximum dosage for more than 2 weeks except under the advice and supervision of a doctor

Directions

- adults and children 12 years of age and over:chew 2-4 tablets completely as symptoms occur, or as directed by a doctor. Do not swallow the tablets whole.
- do not take for symptoms that persist for more than 2 weeks unless advised by a doctor

Other information

- each tablet contains: calcium 300mg
- store at room temperature. Keep the container tightly closed

Inactive ingredients

adipic acid, dextrose, FD&C Blue No. 1 Lake, FD&C Red No. 40 Lake, flavors, magnesium stearate, maltodextrin, starch, sucralose.

Questions?

1-866-467-2748

Safety sealed: Do not use if printed seal under cap is torn or missing

Package/Label Principal Display Panel

NDC# 21130-515-60

*Compare to the active ingredient in Extra Strength Tums® Smoothies™

EXTRA STRENGTH

Smooth Antacid Tablets

Calcium Carbonate USP 750 mg

Fas Relief of Upset Stomach, Heartburn and Acid Indigestion

Assorted Berries

Naturally and Artificially Flavored

60 Chewable Tablets

K PAREVE

GLUTEN- FREE

Distributed by:

*This product is not manufactured or distributed by GlaxoSmithKline, the distributor of Extra Strength Tums® Smoothies™.